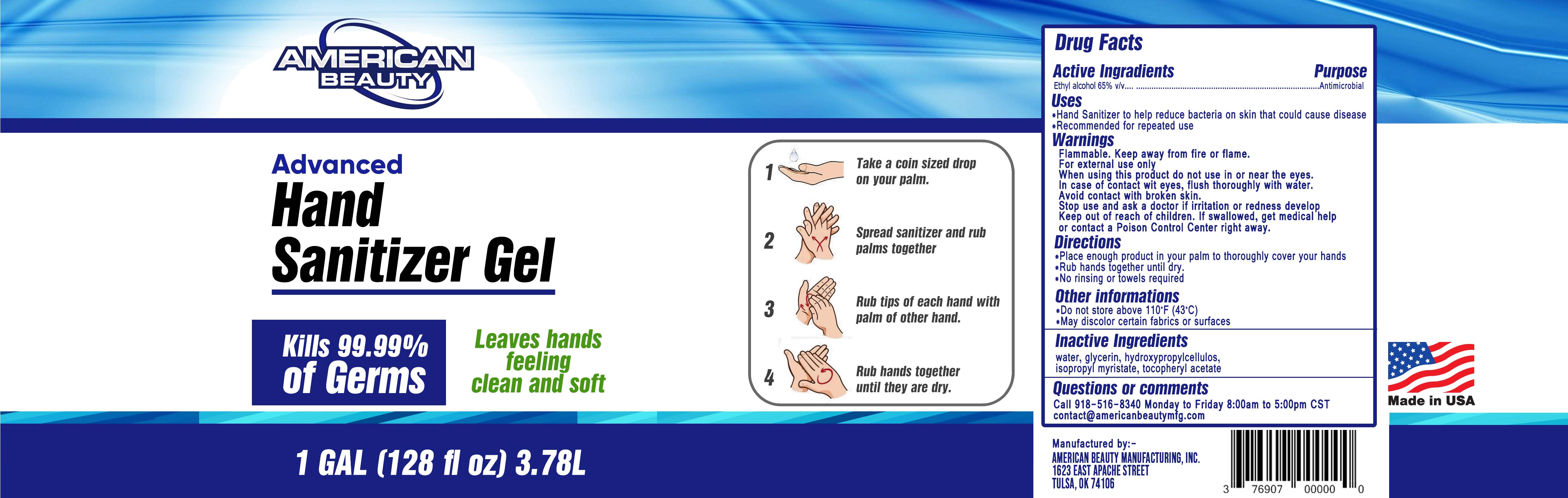 DRUG LABEL: American Beauty Advanced Hand Sanitizer
NDC: 76907-401 | Form: GEL
Manufacturer: American Beauty Manufacturing Inc
Category: otc | Type: HUMAN OTC DRUG LABEL
Date: 20201228

ACTIVE INGREDIENTS: ALCOHOL 2461 mL/3785 mL
INACTIVE INGREDIENTS: ISOPROPYL MYRISTATE 19 mL/3785 mL; GLYCERIN 55 mL/3785 mL; ALPHA-TOCOPHEROL ACETATE 2 mL/3785 mL; WATER 1267 mL/3785 mL; HYDROXYPROPYL CELLULOSE, LOW SUBSTITUTED 34 g/3785 mL

The hand sanitizer is manufactured using only the following United States Pharmacopoeia (USP) grade ingredients in the preparation of the product (percentage in final product formulation)

1. Alcohol (ethanol) (USP or Food Chemical Codex (FCC) grade) (65%, volume/volume (v/v)) in an aqueous solution denatured according to Alcohol and Tobacco Tax and Trade Bureau regulations in 27 CFR part 20.
2. Glycerol (1.45% v/v).
3. Hydroxypropyl Cellulose (1.00% w/w).
4. Aplha-Tocopherol Acetate (0.05% w/w).
5. Isopropyl Myristate (0.50% v/v)
6. Sterile distilled water or boiled cold water.

The firm does not add other active or inactive ingredients. Different or additional ingredients may impact the quality and potency of the product.

Active Ingredient(s)

Alcohol 65% v/v. Purpose: Antiseptic

Purpose

Antiseptic, Hand Sanitizer

Use

Hand Sanitizer to help reduce bacteria that potentially can cause disease.

Recommended for repeated use

Warnings

Flammable. Keep away from fire or flame.

For external use only

When using this product do not use in or near the eyes.

In case of contact with eyes, flush thoroughly with water.

Avoid contact with broken skin.

Stop use and ask a doctor if irritation or redness develop.

Keep out of reach of children. If swallowed, get medical help or contact a Poison Control Center right away.

Directions

- Place enough product in your palm to thoroughly cover your hands
- Rub hands together until dry
- No rinsing or towels required

Inactive ingredients

water, glycerin, hydroxypropylcellulos, isopropyl myristate, tocopheryl acetate

Keep out of reach of children. If swallowed, get medical help or contact a Poison Control Center right away.

QUESTIONS

Call 918-516-8340 Monday to Friday 8:00am to 5:00pm CST

contact@americanbeautymfg.com

OTHER SAFETY INFORMATION

Do not store above 110*F (43*C)

May discolor certain fabrics or surfaces

Package Label - Principal Display Panel

3.78L NDC: 76907-401-01